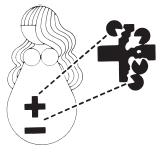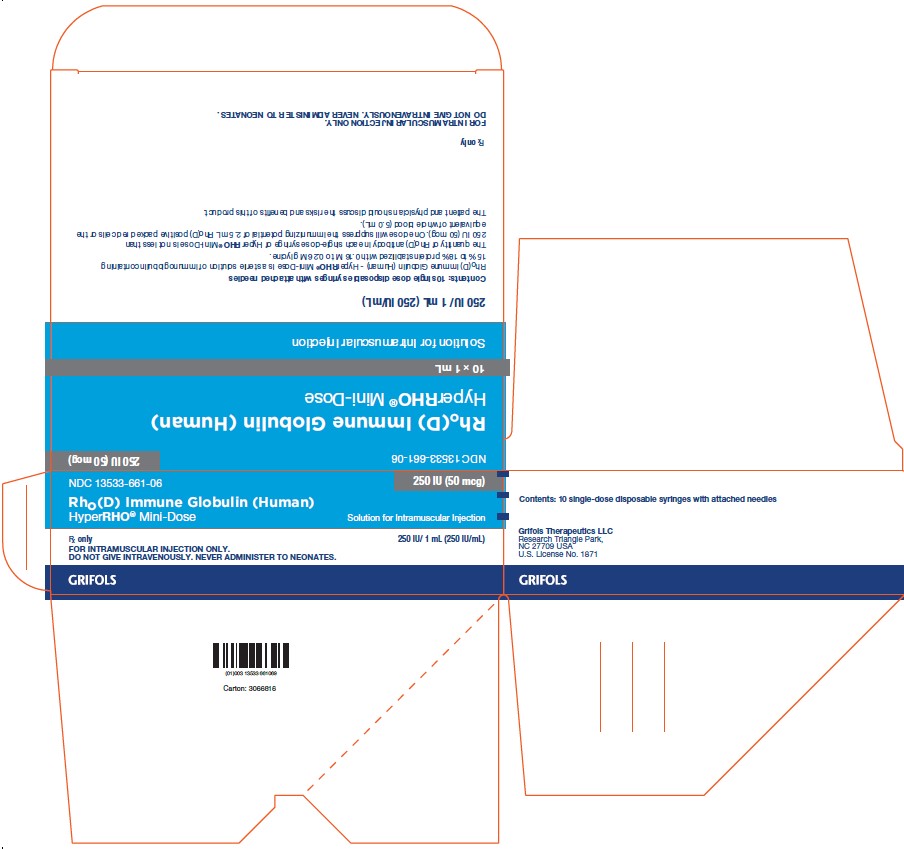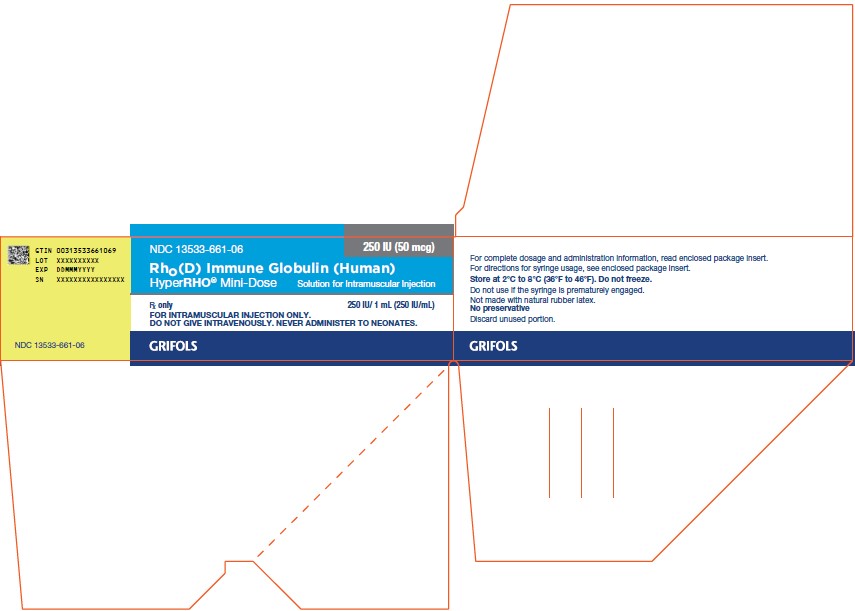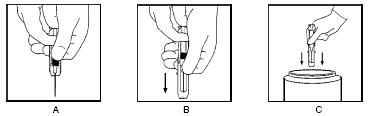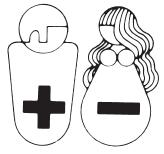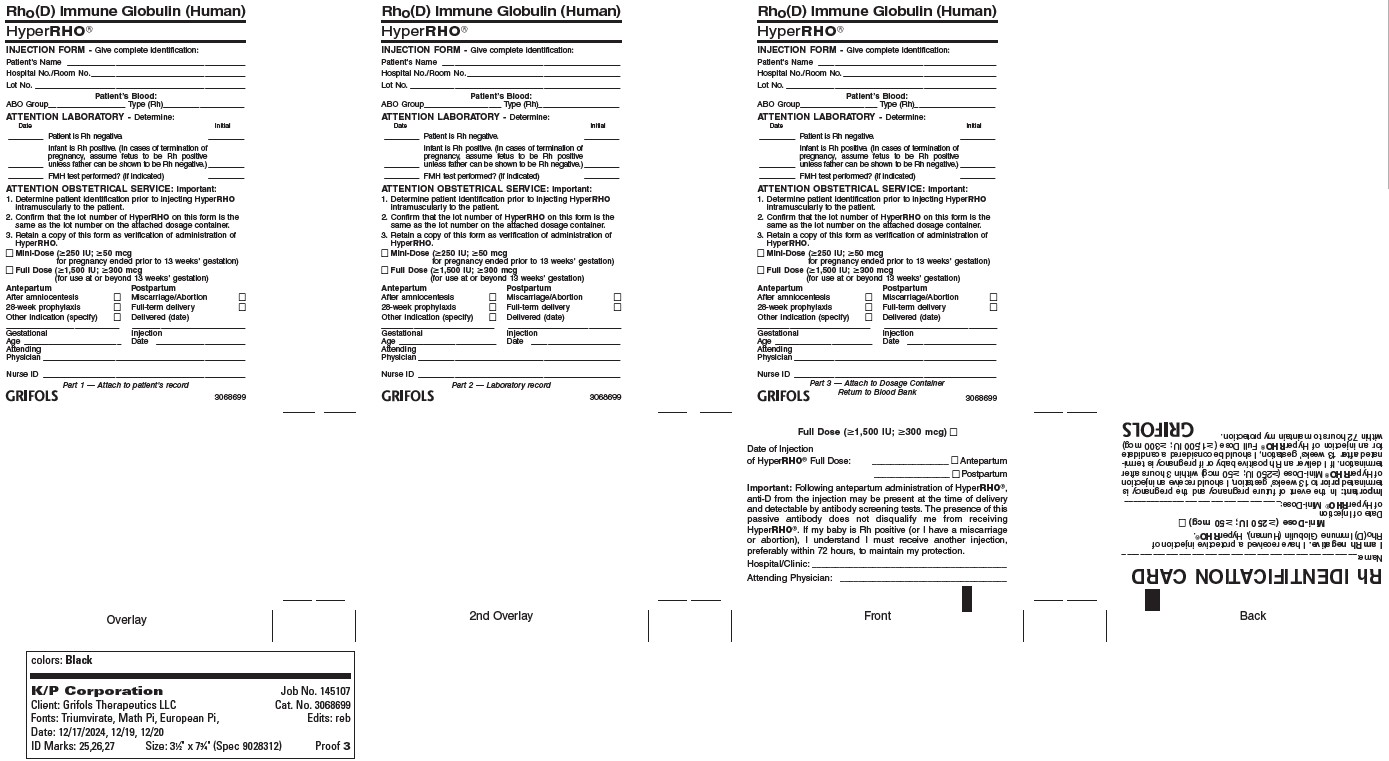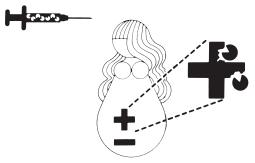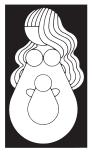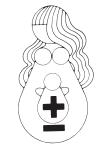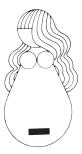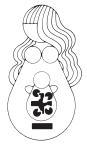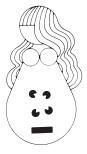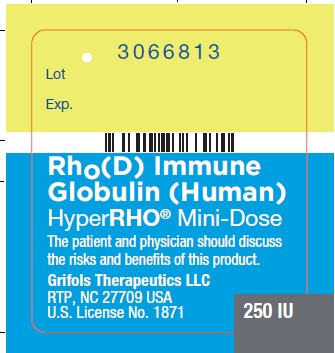 DRUG LABEL: HYPERRHO 
NDC: 13533-661 | Form: SOLUTION
Manufacturer: GRIFOLS USA, LLC
Category: other | Type: PLASMA DERIVATIVE
Date: 20250624

ACTIVE INGREDIENTS: Human Rho(d) Immune Globulin 250 [iU]/1 mL
INACTIVE INGREDIENTS: Glycine; Water

Rho(D) Immune Globulin (Human)
HyperRHO® Mini-Dose

DESCRIPTION

Rho(D) Immune Globulin (Human) — HyperRHO® Mini-Dose is a clear or slightly opalescent and colorless or pale yellow sterile solution of human rho(D) immune globulin containing antibodies to Rho(D) for intramuscular administration; it contains no preservative. HyperRHO Mini-Dose is prepared from pools of human plasma collected from healthy donors by a combination of cold ethanol fractionation, caprylate precipitation and filtration, caprylate incubation, anion exchange chromatography, nanofiltration and low pH incubation. HyperRHO Mini-Dose is formulated as a 15% to 18% protein solution at a pH of 4.1 to 4.8 in 0.16 M to 0.26 M glycine. One dose of HyperRHO Mini-Dose contains not less than one-sixth the quantity of Rho(D) antibody contained in one standard dose of Rho(D) Immune Globulin (Human), and it will suppress the immunizing potential of 2.5 mL of Rho(D) positive packed red blood cells or the equivalent of whole blood (5 mL). The quantity of Rho(D) antibody in HyperRHO Mini-Dose is not less than 250 IU (50 mcg) per 1 mL.

When medicinal biological products are administered, the risk of infectious diseases due to transmission of pathogens cannot be totally excluded. However, in the case of products prepared from human plasma, the risk of transmission of pathogens is reduced by epidemiological surveillance of the donor population and selection of individual donors by medical interview; testing of individual donations and plasma pools; and the presence in the manufacturing processes of steps with demonstrated capacity to inactivate/remove pathogen.

In the manufacturing process of HyperRHO Mini-Dose, there are several steps with the capacity for viral inactivation or removal.(1) The main steps of the manufacturing process that contribute to the virus clearance capacity are as follows:

- Caprylate precipitation/depth filtration
- Caprylate incubation
- Depth filtration
- Column chromatography
- Nanofiltration
- Low pH final container incubation

To provide additional assurance of the pathogen safety of the final product, the capacity of the HyperRHO Mini-Dose manufacturing process to remove and/or inactivate viruses has been demonstrated by laboratory spiking studies on a scaled down process model using a wide range of viruses with diverse physicochemical properties.

The combination of all of the above-mentioned measures provides the final product with a high margin of safety from the potential risk of transmission of infectious viruses.

The caprylate/chromatography manufacturing process was also investigated for its capacity to decrease the infectivity of an experimental agent of transmissible spongiform encephalopathy (TSE), considered as a model for the variant Creutzfeldt-Jakob disease (vCJD) and Creutzfeldt-Jakob disease (CJD) agents.(1) These studies provide reasonable assurance that low levels of CJD/vCJD agent infectivity, if present in the starting material, would be removed by the caprylate/chromatography manufacturing process.

CLINICAL PHARMACOLOGY

Rh sensitization may occur in nonsensitized Rho(D) negative women following transplacental hemorrhage resulting from spontaneous or induced abortions.(2,3) The risk of sensitization is higher in women undergoing induced abortions than in those aborting spontaneously.(3-4)

HyperRHO Mini-Dose is used to prevent the formation of anti-Rho(D) antibody in Rho(D) negative women who are exposed to the Rho(D) antigen at the time of spontaneous or induced abortion (up to 12 weeks’ gestation).(4-6) HyperRHO Mini-Dose suppresses the stimulation of active immunity by Rho(D) positive fetal erythrocytes that may enter the maternal circulation at the time of termination of the pregnancy.

The amount of anti-Rho(D) in HyperRHO Mini-Dose has been shown to effectively prevent maternal isosensitization to the Rho(D) antigens following spontaneous or induced abortion occurring up to the 12th week of gestation.(7-9) After the 12th week of gestation, a standard dose of HyperRHO Full Dose is indicated.

In a clinical study in 12 healthy human adults receiving another hyperimmune immune globulin product, Rabies Immune Globulin (Human), HyperRAB®, prepared by the same manufacturing process, detectable passive antibody titers were observed in the serum of all subjects by 24 hours post injection and persisted through the 21 day study period.

INDICATIONS AND USAGE

HyperRHO Mini-Dose is recommended to prevent the isoimmunization of Rho(D) negative women at the time of spontaneous or induced abortion of up to 12 weeks’ gestation provided the following criteria are met:

1. The mother must be Rho(D) negative and must not already be sensitized to the Rho(D) antigen.
2. The father is not known to be Rho(D) negative.
3. Gestation is not more than 12 weeks at termination.

Note: Rho(D) Immune Globulin (Human) prophylaxis is not indicated if the fetus or father can be determined to be Rh negative. If the Rh status of the fetus is unknown, the fetus must be assumed to be Rho(D) positive, and HyperRHO Mini-Dose should be administered to the mother.

FOR ABORTIONS OR MISCARRIAGES OCCURRING AFTER 12 WEEKS’ GESTATION, A STANDARD DOSE OF Rho(D) IMMUNE GLOBULIN (HUMAN) IS INDICATED.

HyperRHO Mini-Dose should be administered within 3 hours or as soon as possible after spontaneous passage or surgical removal of the products of conception. However, if HyperRHO Mini-Dose is not given within this time period, consideration should still be given to its administration since clinical studies in male volunteers have demonstrated the effectiveness of Rho(D) Immune Globulin (Human) in preventing isoimmunization as long as 72 hours after infusion of Rho(D) positive red cells.(10)

CONTRAINDICATIONS

None known.

WARNINGS

HyperRHO Mini-Dose is made from human plasma. Products made from human plasma may contain infectious agents, such as viruses, the variant Creutzfeldt-Jakob disease (vCJD) agent, and, theoretically, the Creutzfeldt-Jakob Disease (CJD) agent that can cause disease. The risk that such products will transmit an infectious agent has been reduced by screening plasma donors for prior exposure to certain viruses, by testing for the presence of certain current virus infections, and by including manufacturing steps that inactivate and/or remove viruses. Despite these measures, such products can still potentially transmit disease. There is also the possibility that unknown infectious agents may be present in such products. Individuals who receive infusions of blood or plasma products may develop signs and/or symptoms of some viral infections, particularly hepatitis C. ALL infections thought by a physician possibly to have been transmitted by this product should be reported by the physician or other healthcare provider to Grifols Therapeutics LLC [1-800-520-2807].

The physician should discuss the risks and benefits of this product with the patient, before prescribing or administering it to the patient.

NEVER ADMINISTER HYPERRHO MINI-DOSE INTRAVENOUSLY. INJECT ONLY INTRAMUSCULARLY. ADMINISTER ONLY TO WOMEN POSTABORTION OR POSTMISCARRIAGE OF UP TO 12 WEEKS’ GESTATION. NEVER ADMINISTER TO THE NEONATE.

HyperRHO Mini-Dose should be given with caution to patients with a history of prior systemic allergic reactions following the administration of human immune globulin preparations.

The attending physician who wishes to administer HyperRHO Mini-Dose to persons with isolated immunoglobulin A (IgA) deficiency must weigh the benefits of immunization against the potential risks of hypersensitivity reactions. Such persons have increased potential for developing antibodies to IgA and could have anaphylactic reactions to subsequent administration of blood products that contain IgA.

As with all preparations administered by the intramuscular route, bleeding complications may be encountered in patients with thrombocytopenia or other bleeding disorders.

PRECAUTIONS

General

Although systemic reactions to immunoglobulin preparations are rare, epinephrine should be available for treatment of acute anaphylactic symptoms.

Drug Interactions

Other antibodies in the HyperRHO Mini-Dose preparation may interfere with the response to live vaccines such as measles, mumps, polio or rubella. Therefore, immunization with live vaccines should not be given within 3 months after HyperRHO Mini-Dose administration.

Pregnancy

Animal reproduction studies have not been conducted with HyperRHO Mini-Dose. It is also not known whether HyperRHO Mini-Dose can cause fetal harm when administered to a pregnant woman or can affect reproduction capacity.

It should be again noted, however, that HyperRHO Mini-Dose is not indicated for use during pregnancy and it should be administered only postabortion or postmiscarriage.

Pediatric Use

Safety and effectiveness in the pediatric population have not been established.

ADVERSE REACTIONS

Reactions to HyperRHO Mini-Dose are infrequent in Rho(D) negative individuals and consist primarily of slight soreness at the site of injection and slight temperature elevation. While sensitization to repeated injections of human globulin is extremely rare, it has occurred.

DOSAGE AND ADMINISTRATION

NEVER ADMINISTER HYPERRHO MINI-DOSE INTRAVENOUSLY. INJECT ONLY INTRAMUSCULARLY. ADMINISTER ONLY TO WOMEN POSTABORTION OR POSTMISCARRIAGE OF UP TO 12 WEEKS’ GESTATION. NEVER ADMINISTER TO THE NEONATE.

One syringe of HyperRHO Mini-Dose provides sufficient antibody to prevent Rh sensitization to 2.5 mL Rho(D) positive packed red cells or the equivalent (5 mL) of whole blood. This dose is sufficient to provide protection against maternal Rh sensitization for women undergoing spontaneous or induced abortion of up to 12 weeks’ gestation.

Rho(D) Immune Globulin (Human) — HyperRHO® Mini-Dose (250 IU; 50 mcg) should be administered within 3 hours or as soon as possible following spontaneous or induced abortion. If prompt administration is not possible, HyperRHO Mini-Dose should be given within 72 hours following termination of the pregnancy.

HyperRHO Mini-Dose is administered intramuscularly, preferably in the deltoid muscle of the upper arm or lateral thigh muscle. The gluteal region should not be used as an injection site because of the risk of injury to the sciatic nerve.(11)

Parenteral drug products should be inspected visually for particulate matter and discoloration prior to administration, whenever solution and container permit.

HyperRHO Mini-Dose is supplied with a syringe and an attached needle guard for your protection and convenience. Please follow instructions below for proper use of syringe and needle guard.

Directions for Syringe Usage

1. Remove the prefilled syringe from the package. Lift syringe by barrel, not by plunger.
2. Twist the plunger rod clockwise until the threads are seated. Do not use if the syringe is prematurely engaged.
3. With the rubber needle shield secured on the syringe tip, push the plunger rod forward a few millimeters to break any friction seal between the rubber stopper and the glass syringe barrel.
4. Remove the needle shield and expel air bubbles. [Do not remove the rubber needle shield to prepare the product for administration until immediately prior to the anticipated injection time.]
5. Proceed with hypodermic needle puncture.
6. Aspirate prior to injection to confirm that the needle is not in a vein or artery.
7. Inject the medication.
8. Keeping your hands behind the needle, grasp the guard with free hand and slide forward toward needle until it is completely covered and guard clicks into place. If audible click is not heard, guard may not be completely activated. (See Diagrams A and B)
9. Place entire prefilled glass syringe with guard activated into an approved sharps container for proper disposal. (See Diagram C)

A number of factors could reduce the efficacy of this product or even result in an ill effect following its use. These include improper storage and handling of the product after it leaves our hands, diagnosis, dosage, method of administration, and biological differences in individual patients. Because of these factors, it is important that this product be stored properly and that the directions be followed carefully during use.

HOW SUPPLIED

HyperRHO Mini-Dose is available in a single-dose syringe with attached needle. The HyperRHO Mini-Dose package contains 10 single-dose syringes. HyperRHO Mini-Dose contains no preservative and is not made with natural rubber latex.

NDC Number | Size
13533-661-06 | Syringe (10 pack)

STORAGE

Store at 2°C to 8°C (36°F to 46°F). Do not freeze. Do not use after expiration date. Discard unused portion.

CAUTION

Rx only
U.S. federal law prohibits dispensing without prescription.

REFERENCES

1. Barnette D, Roth NJ, Hotta J, et al. Pathogen safety profile of a 10% IgG preparation manufactured using a depth filtration-modified process. Biologicals 2012;40:247-53.
2. Queenan JT, Shah S, Kubarych SF, et al. Role of induced abortion in rhesus immunisation. Lancet 1971;1(7704):815-7.
3. Goldman JA, Eckerling B. Prevention of Rh immunization after abortion with anti-Rho(D)-immunoglobulin. Obstet Gynecol 1972;40(3):366-70.
4. The selective use of Rho(D) immune globulin (RhIG). ACOG Tech Bull 61,1981.
5. Prevention of Rh sensitization. WHO Tech Rep Ser 468, 1971.
6. Recommendation of the Public Health Service Advisory Committee on Immunization Practices. Rh immune globulin. MMWR 1972;21(15):126-7.
7. Stewart FH, Burnhill MS, Bozorgi N. Reduced dose of Rh immunoglobulin following first trimester pregnancy termination. Obstet Gynecol 1978;51(3):318-22.
8. McMaster conference on prevention of Rh immunization. 28-30 September, 1977. Vox Sang 1979;36(1):50-64.
9. Simonovits I. Efficiency of anti-D IgG prevention after induced abortion. Vox Sang 1974;26(4):361-7.
10. Freda VJ, Gorman JG, Pollack W Prevention of Rh-hemolytic disease with Rh-immune globulin. Am J Obstet Gynecol 1977;128(4):456-60.
11. Recommendations of the Advisory Committee on Immunization Practices (ACIP) and the American Academy of Family Physicians (AAFP). General recommendations on immunization. MMWR 2002;51(RR02):1-36.

(Rev. 5/2025)
GRIFOLS
Grifols Therapeutics LLC
Research Triangle Park, NC 27709 USA 3068045
U.S. License No. 1871

PATIENT COUNSELING INFORMATION

The Rh Factor and Your Pregnancy

Information About Pregnancy Protection

The Rh Factor and When It Is Important

The Rh factor is one of many blood group antigens found on the surface of red blood cells. If you have this antigen you are considered Rh positive. If you don’t, then you are considered Rh negative. Everyone is either Rh positive or Rh negative. One type is neither better nor worse than the other, only different.

Your Rh factor is important if you are an Rh negative woman and you become pregnant, or if you receive a blood transfusion.

How the Rh Factor Can Affect Your Future

If you have Rh negative blood, there are two situations that can affect you:

1. If the father of your baby is Rh positive, the baby will probably be Rh positive too. An Rh negative woman carrying an Rh positive baby may have an immune reaction if some of the baby’s Rh positive blood cells enter her bloodstream.
This immune reaction, called isoimmunization, means your body’s defense system recognizes Rh positive blood as foreign from your own and produces “antibodies” to destroy the invading Rh positive blood cells.
The passage of blood from the baby to the mother’s bloodstream happens most often at delivery, but can also occur during miscarriage, the termination of pregnancy, amniocentesis (test performed to determine fetal health), or due to an injury or trauma. It is important to note that a small number of women develop antibodies to Rh positive blood cells during pregnancy for no apparent reason.
Antibodies to Rh positive blood may not be a problem in first pregnancies; however, the antibodies stay in your bloodstream, ready to attack invading Rh positive blood cells, for many years to come. This can lead to problems in future pregnancies by causing miscarriage or a disease known as hemolytic disease of the newborn.
Babies born to Rh positive mothers, regardless of the father’s blood type, will usually be free of the dangers of hemolytic disease.
2. Someday it may become necessary for you to receive a blood transfusion. If Rh positive antibodies already reside in your bloodstream due to isoimmunization and the blood you receive is Rh positive due to error or lifesaving reasons, your Rh positive antibodies will become mobilized and destroy the donor Rh positive cells. As a result, the transfusion could be unsuccessful and possibly harmful to you.

Hemolytic Disease of the Newborn: A Threat to Your Baby

When an Rh negative woman has Rh positive antibodies in her blood and the baby she is carrying is Rh positive, the antibodies could possibly enter the baby’s bloodstream, attack the baby’s red blood cells and cause hemolytic disease of the newborn. At birth, the infant suffering from hemolytic disease may be jaundiced and anemic or suffer permanent damage of the brain and central nervous system which may result in mental retardation, hearing loss, or cerebral palsy. Extensive medical care can be required, including an exchange transfusion, in which all of the baby’s blood is replaced. This usually stops the destruction of the baby’s red blood cells and gives the infant a chance to survive.

The risk of hemolytic disease of the newborn is slight with the first baby, but increases with each successive pregnancy.

Preventing Hemolytic Disease

HyperRHO® , Rho(D) Immune Globulin (Human), can prevent hemolytic disease of the newborn, provided Rh positive antibodies do not already reside in your bloodstream.

HyperRHO is a specially prepared gamma globulin with a high level of preformed antibodies against Rh positive blood cells. The injection of HyperRHO destroys any Rh positive blood cells that may have entered the mother’s bloodstream and prevents the mother’s immune system from producing Rh positive antibodies; thus protecting the baby from developing hemolytic disease.

HyperRHO Full Dose — When Prescribed

Pregnancy and Other Obstetric Conditions Pertaining to Rh Negative Women

HyperRHO Full Dose (1500 IU; 300 mcg) is administered during pregnancy if you fall into a high-risk category. For example, you are at risk of producing Rh positive antibodies if you have an amniocentesis procedure performed, or if you have a miscarriage or other termination of pregnancy at or beyond 13 weeks' gestation.

Laboratory findings have shown that some Rh negative women develop Rh positive antibodies during the last weeks of pregnancy even without an antibody-stimulating event. As a preventive measure, your physician will probably recommend the first injection of HyperRHO Full Dose at the 28th week of pregnancy.

In both of the above situations, if the blood type of the father or baby can be determined to be Rh negative, an injection of HyperRHO is not required.

Another injection of HyperRHO Full Dose is administered within 72 hours of delivery of an Rh positive baby.

Blood Transfusion

HyperRHO Full Dose (1500 IU; 300 mcg) may be used to prevent isoimmunization in Rh negative individuals who have been transfused with Rh positive red blood cells or blood components containing red blood cells.

HyperRHO Mini-Dose — When Prescribed

A single dose of HyperRHO Mini-Dose (250 IU; 50 mcg) may be prescribed for an Rh negative woman instead of HyperRHO Full Dose (1500 IU; 300 mcg) in the event of miscarriage or other termination of pregnancy occurring prior to 13 weeks' gestation. HyperRHO Mini-Dose is not required if the blood type of the father or fetus can be determined to be Rh negative.

Will You Need HyperRHO Again?

HyperRHO provides protection only if you have not already produced Rh positive antibodies. Women who have developed antibodies through previous pregnancy, miscarriage, other termination of pregnancy, or blood transfusion cannot be protected by HyperRHO. This is why with each pregnancy it is important to have HyperRHO injections within the prescribed time period.

Reactions to HyperRHO

You may feel a temporary soreness at the site of the injection. You may also have a slight and temporary change in body temperature. In very rare instances, an allergic type of reaction can occur, for which your physician will take appropriate measures.

Delivering a Sound, Healthy Baby

Your physician can answer any questions you may have about receiving a HyperRHO injection to prevent hemolytic disease of the newborn. If you know that you are Rh negative and you are pregnant, you should discuss your situation with your physician. Today, with HyperRHO, hemolytic disease of the newborn can be reduced to its lowest possible rate of incidence.

GRIFOLS
Grifols Therapeutics LLC
Research Triangle Park, NC 27709 USA 3068045
U.S. License No. 1871 (Rev. 5/2025)

Development of Hemolytic Disease

1 Rh positive (+) father. Rh negative (–) mother. | 2 Pregnancy: Rh– mother is carrying Rh+ baby.
3; The passage of Rh+ blood from the baby to the mother’s bloodstream happens most often at delivery, but can also occur during miscarriage, other termination of pregnancy, amniocentesis, or due to injury or trauma. | 4; Rh+ antibodies stay in your bloodstream, ready to attack invading Rh+ blood cells, for many years to come.
5; Next pregnancy, mother’s Rh+ antibodies enter baby’s Rh+ bloodstream,; attacking baby’s blood cells and causing hemolytic disease of the newborn.

How HyperRHO Immune Globulin Can Prevent Hemolytic Disease

1 You will probably be given two injections of HyperRHO Full Dose, one at the 28th week of your pregnancy and another within 72 hours of delivery, miscarriage or other termination of pregnancy. A single injection of HyperRHO Mini-Dose may be prescribed instead of HyperRHO Full Dose in the event of miscarriage or other termination of pregnancy occurring prior to 13 weeks' gestation. | 2 HyperRHO immunization prevents formation of mother’s own Rh+ antibodies. Mother’s bloodstream remains free of Rh+ antibodies.
3 Next pregnancy, baby develops normally. HyperRHO should be administered following delivery, miscarriage, or other termination of pregnancy to continue protection if baby is Rh+.

PACKAGE LABEL

NDC 13533-661-06
250 IU (50 mcg)
Rho (D) Immune Globulin (Human)
HyperRHO® Mini-Dose
Solution for Intramuscular Injection
250 IU / 1 mL (250 IU/mL)
Rx only
FOR INTRAMUSCULAR INJECTION ONLY.
DO NOT GIVE INTRAVENOUSLY. NEVER ADMINISTER TO NEONATES.
GRIFOLS
Contents: 10 single-dose disposable syringes with attached needles
Grifols Therapeutics LLC
Research Triangle Park,
NC 27709 USA
U.S. License No. 1871
GRIFOLS
NDC 13533-661-06
250 IU (50 mcg)
Rho (D) Immune Globulin (Human)
HyperRHO® Mini-Dose
10 x 1 mL
Solution for Intramuscular Injection
250 IU / 1 mL (250 IU/mL)
Contents: 10 single dose disposable syringes with attached needles
Rho(D) Immune Globulin (Human) - HyperRHO® Mini-Dose is a sterile solution of immunoglobulin containing
15% to 18% protein stabilized with 0.16 M to 0.26 M glycine.
The quantity of Rho(D) antibody in each single-dose syringe of HyperRHO® Mini-Dose is not less than
250 IU (50 mcg). One dose will suppress the immunizing potential of 2.5 mL Rho(D) positive packed red cells or the equivalent of whole blood (5.0 mL).
The patient and physician should discuss the risks and benefits of this product.
Rx only
FOR INTRAMUSCULAR INJECTION ONLY.
DO NOT GIVE INTRAVENOUSLY. NEVER ADMINISTER TO NEONATES.

NDC 13533-661-06
250 IU (50 mcg)
Rho (D) Immune Globulin (Human)
HyperRHO® Mini-Dose
Solution for Intramuscular Injection
250 IU / 1 mL (250 IU/mL)
Rx only
FOR INTRAMUSCULAR INJECTION ONLY.
DO NOT GIVE INTRAVENOUSLY. NEVER ADMINISTER TO NEONATES.
GRIFOLS
For complete dosage and administration information, read enclosed package insert.
For directions for syringe usage, see enclosed package insert.
Store at 2°C to 8°C (36°F to 46°F). Do not freeze.
Do not use if the syringe is prematurely engaged.
Not made with natural rubber latex.
No preservative
Discard unused portion.
GRIFOLS
GTIN 00313533661069
LOT XXXXXXXXXX
EXP DDMMMYYYY
SN XXXXXXXXXXXXXXXX
NDC 13533-661-06

3066813
Lot
Exp.
Rho (D) Immune
Globulin (Human)
HyperRHO® Mini-Dose
The patient and physician should discuss
the risks and benefits of this product.
Grifols Therapeutics LLC
RTP, NC 27709 USA
U.S. License No. 1871
250 IU